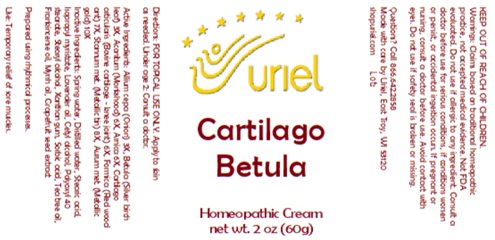 DRUG LABEL: Cartilago Betula
NDC: 48951-3040 | Form: CREAM
Manufacturer: Uriel Pharmacy Inc.
Category: homeopathic | Type: HUMAN OTC DRUG LABEL
Date: 20250627

ACTIVE INGREDIENTS: ONION 3 [hp_X]/1 g; BETULA PUBESCENS LEAF 3 [hp_X]/1 g; ACONITUM NAPELLUS 6 [hp_X]/1 g; ARNICA MONTANA 6 [hp_X]/1 g; BOS TAURUS CARTILAGE 6 [hp_X]/1 g; FORMICA RUFA 7 [hp_X]/1 g; TIN 8 [hp_X]/1 g; GOLD 10 [hp_X]/1 g
INACTIVE INGREDIENTS: WATER; STEARIC ACID; ISOPROPYL MYRISTATE; LAVENDER OIL; CETYL ALCOHOL; POLYOXYL 40 STEARATE; STEARYL ALCOHOL; XANTHAN GUM; TEA TREE OIL; FRANKINCENSE OIL; MYRRH OIL; CITRUS PARADISI SEED; SORBIC ACID

Cartilago Betula

INDICATIONS AND USAGE

Directions: FOR TOPICAL USE ONLY.

DOSAGE AND ADMINISTRATION

Apply to skin as needed. Under age 2: Consult a doctor.

ACTIVE INGREDIENT

Active Ingredients: Allium cepa (Onion) 3X,Betula (Silver birch leaf) 3X, Aconitum (Monkshood) 6X, Arnica 6X, Cartilago articularis (Bovine cartilage - knee joint) 6X, Formica (Red wood ant) 7X, Stannum met. (Metallic tin) 8X, Aurum met. (Metallic gold) 10X

INACTIVE INGREDIENT

Inactive Ingredients: Spring Water, Distilled water,Stearic acid,Isopropyl myristate,Lavender oil, Cetyl alcohol,Polyoxyl 40 stearate, Stearyl alcohol,Xanthan gum,Sorbic acid,Tea tree oil,Frankincense oil,Myrrh oil,Grapefruit seed extract

Prepared using rhythmal processes.

PURPOSE

Use: Temporary relief of sore muscles.

KEEP OUT OF REACH OF CHILDREN.

WARNINGS

Warnings: Claims based on traditional homeopathic practice, not accepted medical evidence. Not FDA evaluated. Do not use if allergic to any ingredient. Consult a doctor before use for serious conditions, if conditions worsen or persist, or accidental ingestion occurs. If pregnant or nursing, consult a doctor before use. Avoid contact with eyes. Do not use if safety seal is broken or missing.

Questions? Call 866.642.2858
Made with care by Uriel, East Troy, WI 53120
shopuriel.com Lot: